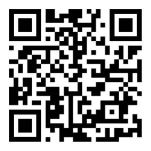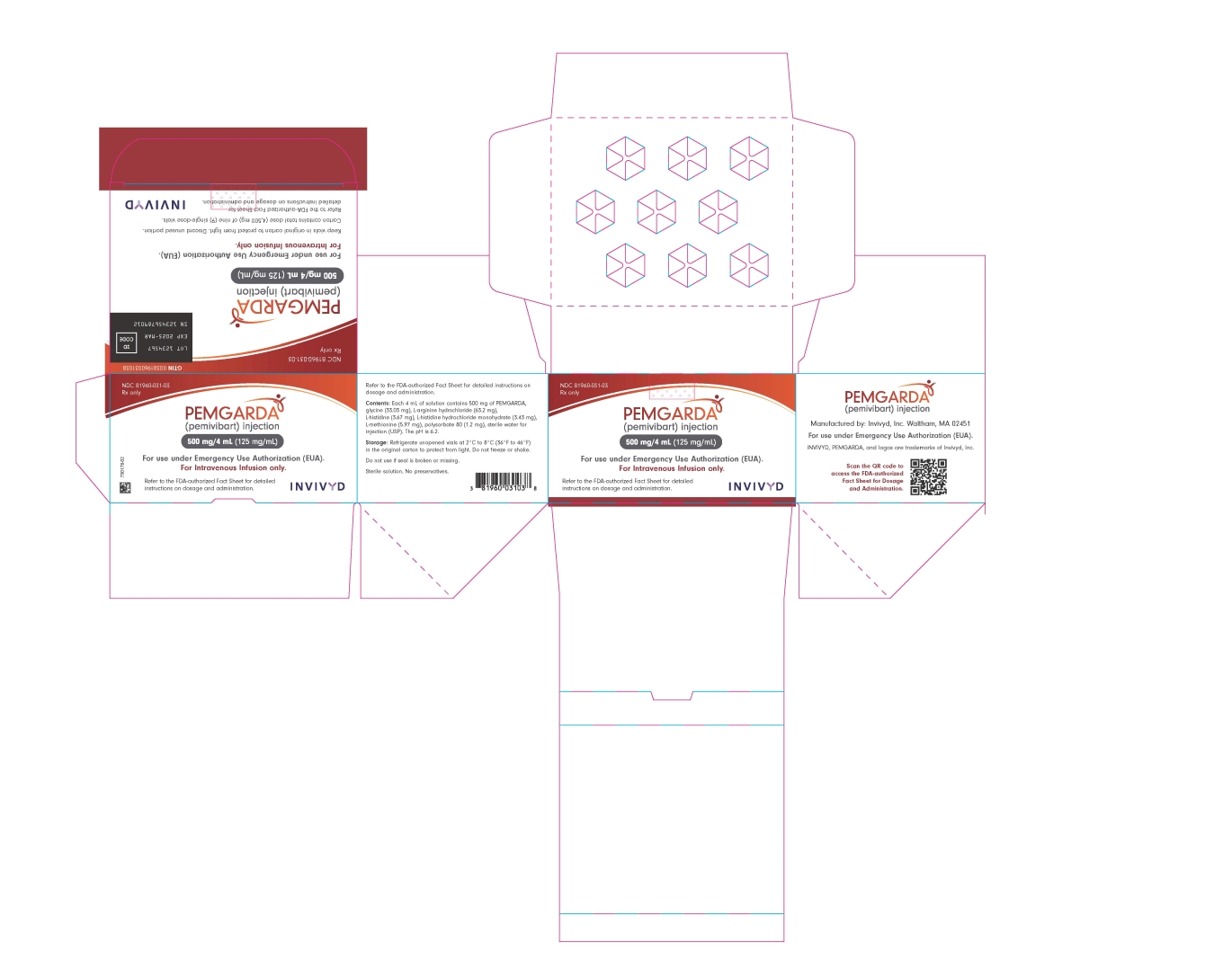 DRUG LABEL: pemgarda
NDC: 81960-031 | Form: INJECTION
Manufacturer: Invivyd, Inc
Category: prescription | Type: HUMAN PRESCRIPTION DRUG LABEL
Date: 20260122

ACTIVE INGREDIENTS: PEMIVIBART 125 mg/1 mL
INACTIVE INGREDIENTS: WATER; GLYCINE; ARGININE HYDROCHLORIDE; POLYSORBATE 80; HISTIDINE MONOHYDROCHLORIDE MONOHYDRATE; METHIONINE; HISTIDINE

HIGHLIGHTS OF PRESCRIBING INFORMATION

FACT SHEET FOR HEALTHCARE PROVIDERS: EMERGENCY USE AUTHORIZATION OF PEMGARDA (PEMIVIBART): These highlights do not include all the information needed to use see full prescribing information for and Initial U.S. Approval

6 ADVERSE REACTIONS

To report SERIOUS ADVERSE REACTIONS or MEDICATION ERRORS potentially related to PEMGARDA (1) do so by submitting FDA Form 3500 online, (2) by downloading this form, and then submitting it by mail or fax, or (3) by contacting the FDA at 1-800-332-1088 to request this form. To report suspected adverse reactions, please also provide a copy of this form to Invivyd, Inc. by email at: pv@invivyd.com or call 1-800-890-3385 to report adverse events.

6.1 Adverse Reactions from Clinical Studies

Cumulatively, infusion site infiltration or extravasation was noted in 5% (15/306) of participants who have moderate-to-severe immune compromise (Cohort A) and in 1% (3/317) of participants in Cohort B with either the first or second dose of PEMGARDA.

To report SERIOUS ADVERSE REACTIONS or MEDICATION ERRORS potentially related to PEMGARDA (1) by submitting FDA Form 3500 online, (2) by downloading this form, and then submitting it by mail or fax, or (3) by contacting the FDA at 1-800-332-1088 to request this form. To report suspected adverse reactions, please also provide a copy of this form to Invivyd, Inc. by email at: pv@invivyd.com or call 1-800-890-3385 to report adverse events.

6.4 Required Reporting for Serious Adverse Events and Medication Errors

To report SERIOUS ADVERSE REACTIONS or MEDICATION ERRORS potentially related to PEMGARDA (1) do so by submitting FDA Form 3500 online, (2) by downloading this form, and then submitting it by mail or fax, or (3) by contacting the FDA at 1-800-332-1088 to request this form. To report suspected adverse reactions, please also provide a copy of this form to Invivyd, Inc. by email at: pv@invivyd.com or call 1-800-890-3385 to report adverse events.

FULL PRESCRIBING INFORMATION

FACT SHEET FOR HEALTHCARE PROVIDERS: EMERGENCY USE AUTHORIZATION OF PEMGARDA (PEMIVIBART)

HIGHLIGHTS OF EMERGENCY USE AUTHORIZATION (EUA)

These highlights of the EUA do not include all the information needed to use PEMGARDA under the EUA. See the FULL FACT SHEET FOR HEALTHCARE PROVIDERS for PEMGARDA.

PEMGARDA (pemivibart) injection, for intravenous use

Original EUA Authorized Date: 03/2024

WARNING: ANAPHYLAXIS

See Full Fact Sheet for Healthcare Providers for the complete boxed warning.

- Anaphylaxis has been observed with PEMGARDA in 0.6% (4/623) of participants in a clinical trial.
- Anaphylaxis was reported during the first and second infusion of PEMGARDA. (5.1, 6.1)
- Anaphylaxis can be life-threatening.
- Prior to administering PEMGARDA, consider the potential benefit of COVID-19 prevention along with the risk of anaphylaxis. (5.1, 6.1, 14)
- Administer PEMGARDA only in settings in which healthcare providers have immediate access to medications to treat anaphylaxis and the ability to activate the emergency medical system (EMS), as necessary.
- Clinically monitor individuals during the infusion and for at least two hours after completion of the infusion.
- Discontinue PEMGARDA use permanently if signs or symptoms of anaphylaxis or any severe systemic reaction are observed and initiate appropriate medications and/or supportive therapy.

---------------------------- RECENT MAJOR CHANGES--------------------------

Microbiology (12.4): Updated viral resistance data 05/2025

Immunogenicity (12.6): Updated with anti-drug antibody data 02/2025

--------------------------- EUA FOR PEMGARDA------------------------------------

The U.S. FDA has issued an EUA for the emergency use of the unapproved product PEMGARDA (pemivibart), a SARS-CoV-2 spike protein-directed attachment inhibitor, for the pre-exposure prophylaxis of coronavirus disease 2019 (COVID-19) in adults and adolescents (12 years of age and older weighing at least 40 kg):

- who are not currently infected with SARS-CoV-2 and who have not had a known recent exposure to an individual infected with SARS‑CoV-2 and:
- who have moderate-to-severe immune compromise due to a medical condition or receipt of immunosuppressive medications or treatments and are unlikely to mount an adequate immune response to COVID-19 vaccination.

PEMGARDA has been authorized by FDA for the emergency use described above. PEMGARDA is not FDA-approved for any use, including use for pre-exposure prophylaxis of COVID-19. (1)

LIMITATIONS OF AUTHORIZED USE

- PEMGARDA is not authorized for use:

-For treatment of COVID-19, or:

-For post-exposure prophylaxis of COVID-19 in individuals who have been exposed to someone infected with SARS‑CoV-2.

- PEMGARDA is authorized for use only when the combined national frequency of variants with substantially reduced susceptibility to PEMGARDA is less than or equal to 90%, based on available information including variant susceptibility to PEMGARDA and national variant frequencies.
- Pre-exposure prophylaxis with PEMGARDA is not a substitute for vaccination in individuals for whom COVID-19 vaccination is recommended. Individuals for whom COVID-19 vaccination is recommended, including individuals with moderate-to-severe immune compromise who may derive benefit from COVID-19 vaccination, should receive COVID-19 vaccination.
- In individuals who have recently received a COVID-19 vaccine, PEMGARDA should be administered at least 2 weeks after vaccination.
- PEMGARDA may only be prescribed for an individual patient by physicians, advanced practice registered nurses, and physician assistants who are licensed or authorized under State law to prescribe drugs.
- PEMGARDA is authorized only for the duration of the declaration that circumstances exist justifying the authorization of the emergency use of PEMGARDA under section 564(b)(1) of the Act, 21 U.S.C. § 360bbb 3(b)(1), unless the authorization is terminated or revoked sooner.

See Full Fact Sheet for Healthcare Providers for examples of medical conditions or treatments that may result in moderate to severe immune compromise and an inadequate immune response to COVID-19 vaccination, the justification for emergency use of drugs during the COVID-19 pandemic, information on available alternatives, and additional information on COVID‑19.

------------------------- DOSAGE AND ADMINISTRATION-----------------------

PEMGARDA must be infused over a minimum of 60 minutes. (2.3) The dosage of PEMGARDA for emergency use in adults and adolescents (12 years of age and older weighing at least 40 kg) is:

Initial Dose: 4500 mg administered as a single intravenous infusion. (2.1)

Repeat Dose: 4500 mg administered as a single intravenous infusion approximately every 3 months. Repeat dosing should be timed from the date of the most recent PEMGARDA dose. (2.1)

See Full Fact Sheet for Healthcare Providers for details on preparation and administration. (2.3)

--------------------- DOSAGE FORMS AND STRENGTHS------------------------

Injection: PEMGARDA 500 mg/4 mL (125 mg/mL) in a single-dose vial. (3)

-------------------------- CONTRAINDICATIONS------------------------------------

PEMGARDA is contraindicated in individuals with previous severe hypersensitivity reactions, including anaphylaxis, to any component of PEMGARDA. (4)

----------------------- WARNINGS AND PRECAUTIONS--------------------------

- Anaphylaxis:Anaphylaxis has been observed with PEMGARDA in 4 of 623 (0.6%) participants in a clinical trial. Administer PEMGARDA only in settings in which healthcare providers have immediate access to medications to treat anaphylaxis and the ability to activate the emergency medical system (EMS), as necessary. If signs or symptoms of an anaphylactic reaction occur, immediately discontinue administration, and initiate appropriate medications and/or supportive therapy. Discontinue PEMGARDA use permanently in individuals who experience signs or symptoms of anaphylaxis. (5.1)
- Hypersensitivity and Infusion-Related Reactions: Hypersensitivity and infusion-related reactions occurring during the infusion and up to 24 hours after the infusion have been observed with PEMGARDA and may be severe or life-threatening. If signs or symptoms of a clinically significant hypersensitivity reaction or infusion-related reaction occur, immediately discontinue administration, and initiate appropriate medications and/or supportive therapy. Clinically monitor individuals during infusion and for at least 2 hours after infusion is complete. (5.2)
- Risk of Cross-Hypersensitivity with COVID-19 Vaccines:PEMGARDA contains polysorbate 80, which is in some COVID‑19 vaccines and is structurally similar to polyethylene glycol (PEG), an ingredient in other COVID-19 vaccines. For individuals with a history of severe hypersensitivity reaction to a COVID-19 vaccine, consider consultation with an allergist-immunologist prior to PEMGARDA administration. (5.3)
- Risk for COVID-19 Due to SARS-CoV-2 Viral Variants with Substantially Reduced Susceptibility to PEMGARDA: Certain SARS-CoV-2 viral variants may emerge that have substantially reduced susceptibility to PEMGARDA. PEMGARDA may not be effective at preventing COVID-19 caused by these SARS-CoV-2 viral variants. Inform individuals of the increased risk, compared to other variants, for COVID-19 due to SARS-CoV-2 viral variants that exhibit significantly reduced susceptibility to PEMGARDA. If signs and symptoms of COVID-19 occur, advise individuals to test for COVID-19 and seek medical attention, including starting treatment for COVID-19 as appropriate. (5.4)

---------------------------------ADVERSE REACTIONS------------------------------

The most common adverse reactions included systemic infusion-related reactions and hypersensitivity reactions, local infusion site reactions, and infusion site infiltration or extravasation. (6.1)

You or your designee must report all SERIOUS ADVERSE EVENTS or MEDICATION ERRORS potentially related to PEMGARDA (1) by submitting FDA Form 3500 online,(2) by downloading this form, and then submitting it by mail or fax, or (3) by contacting the FDA at 1-800-FDA-1088 to request this form. Please also provide a copy of this form to Invivyd, Inc. by email at: pv@invivyd.com or call 1-800-890-3385 to report adverse events. (6.4)

See PATIENT AND PARENTS/CAREGIVER FACT SHEET

TABLE OF CONTENTS*

1 EMERGENCY USE AUTHORIZATION FOR PEMGARDA

2 DOSAGE AND ADMINISTRATION

2.1 Dosage for Emergency Use of PEMGARDA

2.2 Dosage Adjustment in Specific Populations

2.3 Dose Preparation and Administration

3 DOSAGE FORMS AND STRENGTHS

4 CONTRAINDICATIONS

5 WARNINGS AND PRECAUTIONS

5.1 Anaphylaxis

5.2 Hypersensitivity and Infusion-Related Reactions

5.3 Risk of Cross-Hypersensitivity with COVID-19 Vaccines

5.4 Risk for COVID-19 Due to SARS-CoV-2 Viral Variants with Substantially Reduced Susceptibility to PEMGARDA

6 ADVERSE REACTIONS

6.1 Adverse Reactions from Clinical Studies

6.4 Required Reporting for Serious Adverse Events and Medication Errors

7 DRUG INTERACTIONS

8 USE IN SPECIFIC POPULATIONS

8.1 Pregnancy

8.2 Lactation

8.4 Pediatric Use

8.5 Geriatric Use

8.6 Renal Impairment

8.7 Hepatic Impairment

10 OVERDOSAGE

11 DESCRIPTION

12 CLINICAL PHARMACOLOGY

12.1 Mechanism of Action

12.2 Pharmacodynamics

12.3 Pharmacokinetics

12.4 Microbiology

12.6 Immunogenicity

13 NONCLINICAL TOXICOLOGY

13.1 Carcinogenesis, Mutagenesis, Impairment of Fertility

13.2 Animal Toxicology and/or Pharmacology

14 CLINICAL STUDIES

14.1 Overview of Immunobridging Approach

14.2 Pre-exposure Prophylaxis of COVID-19 (VYD222-PREV-001 [CANOPY])

14.3 Overall Benefit-Risk Assessment and Limitations of Data Supporting the Benefits of the Product

16 HOW SUPPLIED/STORAGE AND HANDLING

17 PATIENT COUNSELING INFORMATION

18 MANUFACTURER INFORMATION

*Sections or subsections omitted from the full prescribing information are not listed

WARNING: ANAPHYLAXIS

- Anaphylaxis has been observed with PEMGARDA in 0.6% (4/623) of participants in a clinical trial.
- Anaphylaxis was reported during the first and second infusion of PEMGARDA. (5.1,6.1)
- Anaphylaxis can be life-threatening.
- Prior to administering PEMGARDA, consider the potential benefit of COVID-19 prevention along with the risk of anaphylaxis. (5.1,6.1, 14)
- Administer PEMGARDA only in settings in which healthcare providers have immediate access to medications to treat anaphylaxis and the ability to activate the emergency medical system (EMS), as necessary.
- Clinically monitor individuals during the infusion and for at least two hours after completion of the infusion.
- Discontinue PEMGARDA use permanently if signs or symptoms of anaphylaxis or any severe systemic reaction are observed and initiate appropriate medications and/or supportive therapy.

1 EMERGENCY USE AUTHORIZATION FOR PEMGARDA

The U.S. Food and Drug Administration (FDA) has issued an Emergency Use Authorization (EUA) for the emergency use of the unapproved product PEMGARDA (pemivibart) for the pre-exposure prophylaxis of coronavirus disease 2019 (COVID-19) in adults and adolescents (12 years of age and older weighing at least 40 kg):

- Who are not currently infected with SARS-CoV-2 and who have not had a known recent exposure to an individual infected with SARS-CoV-2 and
- Who have moderate-to-severe immune compromise due to a medical condition or receipt of immunosuppressive medications or treatments and are unlikely to mount an adequate response to COVID-19 vaccination.

Medical conditions or treatments that may result in moderate to severe immune compromise and an inadequate immune response to COVID-19 vaccination include:

- Active treatment for solid tumor and hematologic malignancies
- Hematologic malignancies associated with poor responses to COVID-19 vaccines regardless of current treatment status (e.g., chronic lymphocytic leukemia, non-Hodgkin lymphoma, multiple myeloma, acute leukemia)
- Receipt of solid-organ transplant or an islet transplant and taking immunosuppressive therapy
- Receipt of chimeric antigen receptor (CAR)-T-cell or hematopoietic stem cell transplant (within 2 years of transplantation or taking immunosuppressive therapy)
- Moderate or severe primary immunodeficiency (e.g., common variable immunodeficiency disease, severe combined immunodeficiency, DiGeorge syndrome, Wiskott-Aldrich syndrome)
- Advanced or untreated HIV infection (people with HIV and CD4 cell counts <200/mm^3, history of an AIDS-defining illness without immune reconstitution, or clinical manifestations of symptomatic HIV)
- Active treatment with high-dose corticosteroids (i.e., ≥20 mg prednisone or equivalent per day when administered for ≥2 weeks), alkylating agents, antimetabolites, transplant-related immunosuppressive drugs, cancer chemotherapeutic agents classified as severely immunosuppressive, and biologic agents that are immunosuppressive or immunomodulatory (e.g., B-cell depleting agents)

Limitations of Authorized Use

- PEMGARDA is not authorized for use:

-For treatment of COVID-19, or

-For post-exposure prophylaxis of COVID-19 in individuals who have been exposed to someone infected with SARS-CoV-2.

- PEMGARDA is authorized for use only when the combined national frequency of variants with substantially reduced susceptibility to PEMGARDA is less than or equal to 90%, based on available information including variant susceptibility to PEMGARDA and national variant frequencies [FDA will monitor conditions to determine whether use is consistent with the scope of authorization, referring to available information, including information on variant susceptibility (e.g., Section 12.4 of the authorized Fact Sheet for Healthcare Providers) and CDC variant frequency data available at: https://covid.cdc.gov/covid-data-tracker/#variant-proportions.] .
- Pre-exposure prophylaxis with PEMGARDA is not a substitute for vaccination in individuals for whom COVID-19 vaccination is recommended. Individuals for whom COVID-19 vaccination is recommended, including individuals with moderate-to-severe immune compromise who may derive benefit from COVID-19 vaccination, should receive COVID‑19 vaccination.
- In individuals who have recently received a COVID-19 vaccine, PEMGARDA should be administered at least 2 weeks after vaccination.

PEMGARDA may only be prescribed for an individual patient by physicians, advanced practice registered nurses, and physician assistants that are licensed or authorized under State law to prescribe drugs.

PEMGARDA has been authorized by FDA for the emergency use described above. PEMGARDA is not FDA-approved for any use, including use for pre-exposure prophylaxis of COVID-19.

PEMGARDA is authorized only for the duration of the declaration that circumstances exist justifying the authorization of the emergency use of PEMGARDA under section 564(b)(1) of the FD&C Act, 21 U.S.C. § 360bbb-3(b)(1), unless the authorization is terminated or revoked sooner.

Justification for Emergency Use of Drugs During the COVID‑19 Pandemic:

There is currently an outbreak of coronavirus disease 2019 (COVID‑19) caused by SARS‑CoV‑2, a novel coronavirus. The Secretary of the U.S. Department of Health and Human Services (HHS) has:

- Determined that there is a public health emergency, or significant potential for a public health emergency [See U.S. Department of Health and Human Services, Determination of a Public Health Emergency and Declaration that Circumstances Exist Justifying Authorizations Pursuant to Section 564(b) of the Federal Food, Drug, and Cosmetic Act, 21 U.S.C. § 360bbb-3. February 4, 2020; https://www.federalregister.gov/documents/2020/02/07/2020-02496/determination-of-public-health-emergency. See also U.S. Department of Health and Human Services, Amended Determination of a Public Health Emergency or Significant Potential for a Public Health Emergency Pursuant to Section 564(b) of the Federal Food, Drug, and Cosmetic Act, 21 U.S.C. § 360bbb-3(b). March 15, 2023 (“Amended Determination”); https://www.federalregister.gov/documents/2023/03/20/2023-05609/covid-19-emergency-use-authorization-declaration.] .
- Declared that circumstances exist justifying the authorization of emergency use of drugs and biological products for the prevention or treatment of COVID-19 [See U.S. Department of Health and Human Services, Declaration that Circumstances Exist Justifying Authorizations Pursuant to Section 564(b) of the Federal Food, Drug, and Cosmetic Act, 21 U.S.C. § 360bbb-3, 85 FR 18250 (April 1, 2020); https://www.federalregister.gov/documents/2020/04/01/2020-06905/emergency-use-authorization-declaration. See also Amended Determination (“The declarations issued pursuant to section 564(b)(1) of the FD&C Act that circumstances exist justifying the authorization of emergency use of certain in vitro diagnostics, personal respiratory protective devices, other medical devices and drugs and biological products, as set forth in those declarations, and that are based on the February 4, 2020 determination, remain in effect until those declarations are terminated in accordance with section 564 of the FD&C Act.”).] .

An EUA is an FDA authorization for the emergency use of an unapproved product or unapproved use of an approved product (i.e., drug, biological product, or device) in the United States under certain circumstances including, but not limited to, when the Secretary of HHS declares that there is a public health emergency that affects the national security or the health and security of United States citizens living abroad, and that involves biological agent(s) or a disease or condition that may be attributable to such agent(s). Criteria for issuing an EUA include:

- The biological agent(s) can cause a serious or life-threatening disease or condition.
- Based on the totality of the available scientific evidence (including data from adequate and well controlled clinical trials, if available), it is reasonable to believe that:
  - the product may be effective in diagnosing, treating, or preventing the serious or life-threatening disease or condition; and
  - the known and potential benefits of the product - when used to diagnose, prevent, or treat such disease or condition - outweigh the known and potential risks of the product, taking into consideration the material threat posed by the biological agent(s).
- There is no adequate, approved, and available alternative to the product for diagnosing, preventing, or treating the serious or life-threatening disease or condition.

Information Regarding Available Alternatives for the EUA Authorized Use

There are no adequate, approved, and available alternatives to PEMGARDA for the pre-exposure prophylaxis of COVID-19 in individuals who are unlikely to mount an adequate immune response to COVID-19 vaccination.

For information on clinical studies of PEMGARDA and other therapies for the pre-exposure prophylaxis of COVID-19, see www.clinicaltrials.gov.

2 DOSAGE AND ADMINISTRATION

2.1 Dosage for Emergency Use of PEMGARDA

Initial Dosing:

The initial dosage of PEMGARDA in adults and adolescents (12 years of age and older weighing at least 40 kg) is 4500 mg administered as a single intravenous (IV) infusion [see Clinical Pharmacology (12.3)].

Repeat Dose:

The repeat dosage is 4500 mg of PEMGARDA administered as a single IV infusion every 3 months. Repeat dosing should be timed from the date of the most recent PEMGARDA dose.

The recommendations for dosing are based on the totality of the scientific evidence including clinical pharmacology data, antiviral activity data, and clinical study data [see Clinical Pharmacology (12.3), Microbiology (12.4), and Clinical Studies (14)].

2.2 Dosage Adjustment in Specific Populations

No dosage adjustment is recommended in pregnant or lactating individuals, in geriatrics, or in individuals with renal or hepatic impairment [see Use in Specific Populations (8)].

2.3Dose Preparation and Administration

General Information:

- PEMGARDA should be prepared and administered by a qualified healthcare provider using aseptic technique .
- Vials of PEMGARDA are for one-time use only.
- Visually inspect the vials for particulate matter and discoloration. PEMGARDA is a clear to slightly opalescent, colorless to yellow solution. Discard the vial if the solution is cloudy, discolored, or if visible particles are observed.
- PEMGARDA should be administered as an IV infusion diluted with 0.9% sodium chloride.

Materials Needed:

- 9 single-dose vials of PEMGARDA (125 mg/mL)
- 50 mL prefilled bag of 0.9% sodium chloride (normal saline) for IV injection
- IV extension set with inline 0.2-micron filter
- Infusion pump or gravity infusion set
- 0.9% sodium chloride injection for flushing

Preparation:

- Remove PEMGARDA vials from refrigerated storage and allow to equilibrate to room temperature (18℃ to 26℃ [64℉ to 79℉]) for 10 minutes before preparation. Do not expose to direct heat. Do not shake vials. Inspect the vials.
- Prepare IV bag by removing and discarding 36 mL from a 50 mL prefilled bag of 0.9% sodium chloride for IV injection.
- Withdraw 36 mL of PEMGARDA from nine (9) vials into appropriately sized polypropylene syringe(s) (e.g., one 40 mL syringe or two 20 mL syringes) and inject into prepared 0.9% sodium chloride IV bag.
- The final product for administration will contain 50 mL: 36 mL of PEMGARDA and 14 mL of 0.9% sodium chloride.
- This product is preservative-free and therefore should be administered immediately.
- If immediate administration is not possible, the diluted solution may be stored at room temperature under ambient light for up to 4 hours. Do not shake the diluted solution.

Administration:

- PEMGARDA should only be administered in settings in which healthcare providers have immediate access to medications to treat a severe hypersensitivity reaction, such as anaphylaxis, and the ability to activate the emergency medical system (EMS), as necessary [see Warnings and Precautions (5.1)].
- Attach infusion set including inline 0.2-micron filter to prepared IV bag, then prime the infusion set.
- Administer the entire 50 mL infusion using infusion pump or gravity infusion set over a minimum of 60 minutes. Due to potential overfill, the entire contents of prepared IV bag should be administered to avoid underdosing.
- Once infusion is complete, flush line with 0.9% sodium chloride.
- Clinically monitor patients during infusion and observe patients for at least 2 hours after infusion is complete [see Warnings and Precautions (5.1)].

3 DOSAGE FORMS AND STRENGTHS

PEMGARDA is a sterile, preservative-free, clear to slightly opalescent, colorless to yellow solution available as:

- Injection: 500 mg/4 mL (125 mg/mL) in a single-dose vial

4 CONTRAINDICATIONS

PEMGARDA is contraindicated in individuals with previous severe hypersensitivity reactions, including anaphylaxis, to any component of PEMGARDA.

5 WARNINGS AND PRECAUTIONS

5.1 Anaphylaxis

Anaphylaxis has been observed with PEMGARDA in 4 of 623 (0.6%) participants in a clinical trial [see Adverse Reactions (6.1)]. Two participants had anaphylaxis during the first infusion, and two participants had anaphylaxis during the second infusion. Anaphylaxis can be life-threatening, and two of the anaphylactic reactions in the clinical trial were reported as life-threatening. Manifestations included pruritus, flushing, urticaria, erythema, angioedema, diaphoresis, dizziness, tinnitus, wheezing, dyspnea, chest discomfort, and tachycardia. In all 4 cases, PEMGARDA was permanently discontinued.

Prior to administering PEMGARDA, consider the potential benefit of COVID-19 prevention along with the risk of anaphylaxis [see Adverse Reactions (6.1), and Clinical Studies (14)].

Administer PEMGARDA only in settings in which healthcare providers have immediate access to medications to treat anaphylaxis and the ability to activate the emergency medical system (EMS), as necessary.

Clinically monitor individuals during the 60-minute infusion and for at least two hours after completion of the infusion. If signs or symptoms of an anaphylactic reaction occur, immediately discontinue administration, and initiate appropriate medications and/or supportive therapy. Discontinue PEMGARDA use permanently in individuals who experience signs or symptoms of anaphylaxis [see Contraindications (4)].

5.2 Hypersensitivity and Infusion-Related Reactions

Hypersensitivity and infusion-related reactions occurring during the infusion and up to 24 hours after the infusion have been observed with administration of PEMGARDA. Hypersensitivity or infusion-related reactions may be severe or life threatening. If signs or symptoms of a clinically significant hypersensitivity or infusion-related reaction occur, immediately discontinue administration, and initiate appropriate medications and/or supportive therapy. Signs and symptoms of hypersensitivity or infusion-related reactions may include:

- Fever, difficulty breathing, reduced oxygen saturation, chills, fatigue, arrhythmia (e.g., atrial fibrillation, sinus tachycardia, bradycardia), chest pain or discomfort, weakness, altered mental status, nausea, headache, bronchospasm, hypotension, hypertension, angioedema, throat irritation, rash including urticaria, pruritus, myalgia, vasovagal reactions (e.g., pre-syncope, syncope), dizziness, and diaphoresis.

If a mild infusion-related reaction occurs, consider slowing or stopping the infusion and administer appropriate medications and/or supportive care. Clinically monitor individuals during infusion and for at least two hours after completion of the infusion for signs and symptoms of hypersensitivity.

Hypersensitivity reactions occurring more than 24 hours after the infusion have also been reported with the use of SARS-CoV-2 monoclonal antibodies under Emergency Use Authorization.

5.3 Risk of Cross-Hypersensitivity With COVID-19 Vaccines

PEMGARDA contains polysorbate 80, which is in some COVID-19 vaccines and is structurally similar to polyethylene glycol (PEG), an ingredient in other COVID-19 vaccines [see Description (11)]. For individuals with a history of a severe hypersensitivity reaction to a COVID-19 vaccine, consider consultation with an allergist-immunologist prior to PEMGARDA administration.

Administration of PEMGARDA should be done under the supervision of a healthcare provider with appropriate medical support to manage severe hypersensitivity reactions. If signs and symptoms of a clinically significant hypersensitivity reaction or anaphylaxis occur during administration of PEMGARDA, immediately discontinue administration and initiate appropriate medications and/or supportive care. Clinically monitor individuals after infusion and observe for at least two hours.

5.4 Risk for COVID-19 Due to SARS-CoV-2 Viral Variants with Substantially Reduced Susceptibility to PEMGARDA

Certain SARS-CoV-2 viral variants may emerge that have substantially reduced susceptibility to PEMGARDA. PEMGARDA may not be effective at preventing COVID-19 caused by these SARS‑CoV-2 viral variants. The cell culture neutralization activity of PEMGARDA against SARS-CoV-2 viral variants is described in Microbiology (12.4).

Inform individuals of the increased risk, compared to other variants, for COVID-19 due to emergent SARS-CoV-2 viral variants that exhibit substantially reduced susceptibility to PEMGARDA. If signs or symptoms of COVID-19 occur, advise individuals to test for COVID-19 and seek medical attention, including starting treatment for COVID-19 as appropriate. Symptoms of COVID-19 may include fever or chills, cough, shortness of breath or difficulty breathing, fatigue, muscle or body aches, headache, new loss of taste or smell, sore throat, congestion or runny nose, nausea or vomiting, or diarrhea. [For additional information on the symptoms of COVID-19, please see https://www.cdc.gov/coronavirus/2019-ncov/symptoms-testing/symptoms.html.]

6 ADVERSE REACTIONS

6.1 Adverse Reactions from Clinical Studies

The following adverse reactions have been observed in the clinical study of PEMGARDA that supported the EUA [see Clinical Studies (14)]. The adverse reaction rates observed in the clinical study cannot be directly compared to rates in the clinical studies of other products and may not reflect the rates observed in clinical practice. Additional adverse reactions associated with PEMGARDA may become apparent with more widespread use.

The safety of PEMGARDA is based on exposure of 623 participants who received at least one dose of PEMGARDA 4500 mg IV in one of two cohorts in the ongoing CANOPY trial. Cohort A is a single-arm, open-label trial in adults who have moderate-to-severe immune compromise (n=306), while Cohort B is a randomized, placebo-controlled trial in which adults who do not have moderate-to-severe immune compromise received PEMGARDA (n=317) or placebo (n=162). In Cohort A, 297 participants received a second dose of PEMGARDA 4500 mg IV three months after the initial dose. In Cohort B, 296 participants received a second dose of PEMGARDA 4500 mg IV and 154 received a second dose of placebo three months after the initial dose.

Anaphylaxis

Anaphylaxis was observed in 4 of 623 (0.6%) participants in CANOPY, all in Cohort A.

Two participants had anaphylaxis during the first infusion, and two participants had anaphylaxis during the second infusion. All four reactions led to permanent discontinuation of PEMGARDA. Three participants had complete resolution, and one participant had acute resolution with sequelae related to a flare of an underlying condition.

Symptoms of anaphylaxis during the first dose included dyspnea, diaphoresis, erythema (face), chest discomfort, and tachycardia in one participant, and flushing, dizziness, tinnitus, and wheezing in one participant. Treatment for both included diphenhydramine.

Both instances of anaphylaxis with the second dose were reported as life-threatening. Symptoms during the second infusion and following discontinuation of the infusion in both participants included pruritus, urticaria, angioedema, dyspnea, and either erythema or flushing. One participant also experienced headache, dizziness, and chest pain; additionally, pruritus, erythema, and urticaria reoccurred in this participant within 24 hours of the initial onset of anaphylaxis. Both participants were treated with diphenhydramine and epinephrine, and one participant also received oral prednisone and metoprolol for an associated flare of an underlying condition.

Systemic Infusion-Related Reactions and Hypersensitivity Reactions

First Dose

Systemic infusion-related reactions and hypersensitivity reactions (i.e., adverse events assessed as causally related) were observed with the first dose in CANOPY in 4% (24/623) of participants who received PEMGARDA across cohorts, including:

- 7% (20/306) of participants who have moderate-to-severe immune compromise (Cohort A), and
- 1% (4/317) of participants who received PEMGARDA in Cohort B

Infusion-related reactions and hypersensitivity reactions were not observed in any participants who received placebo in Cohort B.

Systemic infusion-related or hypersensitivity reactions that started within 24 hours of the first dose of PEMGARDA treatment were reported as infusion-related reaction, infusion-related hypersensitivity, hypersensitivity, fatigue, headache, tachycardia, dermatitis, diarrhea, myalgia, nausea, paresthesia, presyncope, and tremor. All reactions were mild or moderate, but two reactions were anaphylaxis [see Box Warnings, and Warnings and Precautions (5.1,5.2)]. Infusion-related reactions or hypersensitivity reactions led to discontinuation of the first infusion in 1% (6/623) of participants who received PEMGARDA.

First and Second Dose, Cumulative

Cumulatively, infusion-related reactions and hypersensitivity reactions were observed in 6% (38/623) of participants across cohorts, including:

- 9% (27/306) of participants who have moderate-to-severe immune compromise (Cohort A).
- 3% (11/317) of participants who received PEMGARDA in Cohort B.

The severity of the reactions was generally mild (24/38) or moderate (12/38), but two reactions, both in Cohort A, were life-threatening [see Boxed Warnings and Warnings and Precautions (5.1,5.2)].

Infusion-related reactions or hypersensitivity reactions led to discontinuation of the first or second infusion in 1% (10/623) of participants who received PEMGARDA across cohorts, including:

- 2% (7/306) of participants who have moderate-to-severe immune compromise (Cohort A).
- 1% (3/317) of participants who received PEMGARDA in Cohort B.

Cumulatively, infusion-related reactions and hypersensitivity reactions were observed following both the first and second dose of PEMGARDA in 1% (7/623) of participants who received PEMGARDA across cohorts, including:

- 2% (6/306) of participants who have moderate-to-severe immune compromise (Cohort A).
- <1% (1/317) of participants who received PEMGARDA in Cohort B.

Local Infusion Site Reactions

First and Second Dose, Cumulative

Cumulatively, local infusion site reactions were observed in 2% (6/306) of participants who have moderate-to-severe immune compromise (Cohort A) with either the first or second dose of PEMGARDA. No local infusion site reactions were observed in Cohort B. Local reactions were reported as infusion site bruising, infusion site erythema, and injection site reaction. All local reactions were mild, and none led to treatment discontinuation.

Cumulatively, infusion site infiltration or extravasation was noted in 5% (15/306) of participants who have moderate-to-severe immune compromise (Cohort A) and in 1% (3/317) of participants in Cohort B with either the first or second dose of PEMGARDA.

Other Common Adverse Events

First and Second Dose, Cumulative

In addition to systemic and local infusion-related/hypersensitivity reactions described above, the most common (≥2%) treatment-emergent adverse events, irrespective of causality, observed with PEMGARDA through Month 6 were as follows:

- In participants who have moderate-to-severe immune compromise in Cohort A: viral infection (7%), upper respiratory tract infection (7%), influenza-like illness (4%), urinary tract infection (4%), fatigue (3%), headache (3%), sinusitis (3%), nasopharyngitis (2%), influenza (2%), and pneumonia (2%).
- In Cohort B: upper respiratory tract infection (8%), viral infection (6%), influenza-like illness (5%), enterovirus infection (3%), and viral upper respiratory tract infection (2%). These adverse events were observed at a similar or higher rate with placebo.

6.4 Required Reporting for Serious Adverse Events and Medication Errors

The prescribing healthcare provider and/or the provider’s designee is/are responsible for mandatory reporting of all serious adverse events* and medication errors potentially related to PEMGARDA within 7 calendar days from the healthcare provider’s awareness of the event, using FDA Form 3500 (for information on how to access this form, see below). The FDA requires that such reports, using FDA Form 3500, include the following:

- Patient demographics and baseline characteristics (e.g., patient identifier, age or date of birth, sex, weight, ethnicity, and race).
- A statement “PEMGARDA use for the pre-exposure prophylaxis of COVID-19 under Emergency Use Authorization (EUA)” under the “Describe Event, Problem, or Product Use/Medication Error”heading.
- Information about the serious adverse event or medication error (e.g., signs and symptoms, test/laboratory data, complications, timing of drug initiation in relation to the occurrence of the event, duration of the event, treatment required to mitigate the event, evidence of event improvement/disappearance after stopping or reducing the dosage, evidence of event reappearance after reintroduction, clinical outcomes).
- Patient’s preexisting medical conditions and use of concomitant products.
- Information about the product (e.g., dosage, route of administration, NDC #).

Submit serious adverse event and medication error reports using FDA Form 3500 to FDA MedWatch using one of the following methods:

- Complete and submit the report online: www.fda.gov/medwatch/report.htm.
- Complete and submit a postage-paid FDA Form 3500
  (https://www.fda.gov/media/76299/download) and return by:
  - Mail to MedWatch, 5600 Fishers Lane, Rockville, MD 20852-9787, or
  - Fax to 1-800-FDA (332)-0178, or
- Call 1-800-FDA (332)-1088 to request a reporting form.

In addition, please provide a copy of all FDA MedWatch forms to:

Invivyd, Inc.
Email: pv@invivyd.com
Or call Invivyd, Inc. at 1-800-890-3385 to report serious adverse events.

The prescribing healthcare provider and/or the provider’s designee is/are responsible for mandatory responses to requests from FDA for information about serious adverse events and medication errors following receipt of PEMGARDA.

*Serious adverse events are defined as:

- Death
- A life-threatening adverse event
- Inpatient hospitalization or prolongation of existing hospitalization
- A persistent or significant incapacity or substantial disruption of the ability to conduct normal life functions
- A congenital anomaly/birth defect
- Other important medical events, which may require a medical or surgical intervention to prevent death, a life-threatening event, hospitalization, disability, or congenital anomaly

7 DRUG INTERACTIONS

Drug-drug interaction studies have not been performed. PEMGARDA is not renally excreted or metabolized by cytochrome P450 enzymes; therefore, interactions with concomitant medications that are renally excreted or that are substrates, inducers, or inhibitors of cytochrome P450 enzymes are unlikely [see Clinical Pharmacology (12.3)].

8 USE IN SPECIFIC POPULATIONS

8.1 Pregnancy

Risk Summary:

There are insufficient data to evaluate a drug-associated risk of major birth defects, miscarriage, or adverse maternal or fetal outcomes. PEMGARDA should only be used during pregnancy if the potential benefit outweighs the potential risk for the mother and the fetus.

Nonclinical reproductive toxicity studies have not been performed with pemivibart. In tissue cross-reactivity studies using human fetal tissues, no off-target binding was detected for pemivibart. Human immunoglobulin G1 (IgG1) antibodies are known to cross the placental barrier; therefore, pemivibart has the potential to be transferred from the mother to the developing fetus. It is unknown whether the potential transfer of pemivibart provides any treatment benefit or risk to the developing fetus.

The estimated background risk of major birth defects and miscarriage for the indicated population is unknown. All pregnancies have a background risk of birth defect, loss, or other adverse outcomes. In the US general population, the estimated background risk of major birth defects and miscarriage in clinically recognized pregnancies is 2% to 4% and 15% to 20%, respectively.

8.2 Lactation

Risk Summary:

There are no available data on the presence of PEMGARDA in human or animal milk, the effects on the breastfed infant, or the effects on milk production. Maternal IgG is known to be present in human milk. The developmental and health benefits of breastfeeding should be considered along with the mother’s clinical need for PEMGARDA and any potential adverse effects on the breastfed infant from PEMGARDA.

8.4 Pediatric Use

PEMGARDA is not authorized for use in pediatrics less than 12 years of age or weighing less than 40 kg. The safety and effectiveness of PEMGARDA has not been established in pediatrics.

The recommended dosing regimen is expected to result in comparable serum exposures of pemivibart in adolescents 12 years of age and older and weighing at least 40 kg as observed in adults, since adults with similar body weight have been included in the CANOPY study [see Adverse Reactions (6.1) and Clinical Studies (14)].

8.5 Geriatric Use

Of the 623 participants who received PEMGARDA in the CANOPY trial, 156 (25%) were aged ≥65 years and 31 (5%) were aged ≥75 years. Based on population pharmacokinetic (PK) analyses, there was no clinically meaningful difference of age on the PK of pemivibart.

8.6 Renal Impairment

PEMGARDA is not eliminated intact in the urine, thus renal impairment is not expected to affect the exposure of pemivibart. Similarly, dialysis is not expected to impact the PK of pemivibart.

8.7 Hepatic Impairment

The effect of hepatic impairment on the PK of pemivibart is unknown.

10 OVERDOSAGE

Doses above 4500 mg PEMGARDA (the authorized dose of pemivibart) were not administered in clinical studies. There is no specific treatment for overdose with PEMGARDA.

11 DESCRIPTION

Pemivibart is a human IgG1 mAb produced by a Chinese Hamster Ovary cell line and has a molecular weight of 147.51 kDa.

PEMGARDA (pemivibart) injection is a sterile, preservative-free, clear to slightly opalescent, colorless to yellow solution for intravenous infusion after dilution. Each 4 mL of solution contains 500 mg of pemivibart, glycine (33.03 mg), L-arginine hydrochloride (63.2 mg), L‑histidine (3.67 mg), L-histidine hydrochloride monohydrate (3.43 mg), L-methionine (5.97 mg), polysorbate 80 (1.2 mg), sterile water for injection (USP). The pH is 6.2.

12 CLINICAL PHARMACOLOGY

12.1Mechanism of Action

Pemivibart is a SARS-CoV-2 antiviral drug [see Microbiology (12.4)].

12.2 Pharmacodynamics

Available data suggest a positive relationship between serum neutralizing antibody titers and COVID-19 pre-exposure-prophylactic efficacy using clinical data (completed prior to the emergence of Omicron and Omicron lineage VOCs) and drug concentration data of neutralizing human monoclonal antibodies against SARS-CoV-2.

Following single-dose administration of pemivibart 4500 mg IV, calculated geometric mean titer values (pemivibart concentration divided by the pseudotyped virus-like particle neutralization assay EC50 value against JN.1) [ see Microbiology (12.4) ] range from 2839 (on Day 90) to 20246 (end of infusion on Day 1). After the repeat dose of pemivibart 4500 mg IV every 3 months, it is anticipated that the range of titers at steady-state will be approximately 33% higher than those observed following the first dose administration.

12.3 Pharmacokinetics

A summary of PK parameters of pemivibart following administration of a single 4500 IV dose of pemivibart to adults based on population PK modeling is provided in Table 1.

Table 1. Summary Statistics of Population PK Parameters of Pemivibart Following a Single 4500 mg Intravenous Dose in Adults

Parameter | Pemivibart
Cmax(μg/mL) | 1820 (18.4)
CDay 28(μg/mL) | 468 (23.9)
CDay 90(μg/mL) | 188 (40.4)
AUC0-3 months(days × μg/mL) | 40500 (22.5)
T1/2(days) | 49.0 (18.4-190)
Accumulation ratio | 1.33
CL (L/d) | 0.0862 (31.1)
Vss(L) | 5.62 (17.3)
Metabolism | Catabolic pathways; same manner as endogenous IgG
Excretion | Not likely to undergo renal excretion

AUC0-3months= area under the serum concentration-time curve from Day 0 to Month 3; CL=renal clearance; Cmax=maximum concentration; PK=pharmacokinetic; T1/2=half-life; Vss=steady state volume of distribution.

Note: All values presented as geometric mean (% coefficient of variation), except for T1/2, which is presented as median (min, max), and for accumulation ratio, which is represented as median. Numerical values are post-hoc PK parameter estimates for participants enrolled in Phase 3 CANOPY.

Specific Populations:

The PK of pemivibart was not substantially affected by age, sex, or race based on a population PK analysis to the pooled data from VYD222-1-001 and Phase 3 CANOPY. Body weight is not expected to have a clinically relevant effect on the PK of pemivibart in individuals with body weights ranging from 43 to 190 kg through 3 months postdose.

Patients with Immune Compromise

Population PK analysis showed immune compromise status had no clinically relevant effect on the PK of pemivibart.

Pediatric Patients

The PK of pemivibart in pediatric individuals has not been evaluated. The dosing regimen is expected to result in comparable plasma exposures of pemivibart in pediatric individuals 12 years of age or older who weigh at least 40 kg as observed in adult individuals [see Use in Specific Populations (8.4)].

Patients with Renal Impairment

Renal impairment is not expected to impact the PK of pemivibart since mAbs with molecular weight >69 kDa are known not to undergo renal elimination. Similarly, dialysis is not expected to impact the PK of pemivibart.

Patients with Hepatic Impairment

Pemivibart is not anticipated to be impacted by hepatic impairment. Pemivibart is expected to be degraded into small peptides and amino acids via catabolic pathways in the same manner as other IgG mAbs and human endogenous IgG antibodies.

12.4 Microbiology

Mechanism of Action:

Pemivibart is a recombinant human monoclonal IgG1λ antibody that targets the SARS-CoV-2 spike protein receptor binding domain (RBD), thereby inhibiting virus attachment to the human angiotensin-converting enzyme 2 (ACE2) receptor on host cells. Amino acid substitutions in the Fc region (M435L/N441A) of pemivibart extend serum half-life. Pemivibart binds the spike RBD proteins of ancestral SARS‑CoV-2 B.1 (D614G) and Omicron variants BA.1, BA.2, and BA.4/5 with equilibrium dissociation constants (KD) of 2.1 nM, 18 nM, 13.5 nM, and 15.9 nM, respectively, and blocks attachment of ancestral SARS-CoV-2 and BA.2.86 variant RBD proteins to the human ACE2 receptor with IC50 values of 0.068 nM (10 ng/mL) and 23 nM (3,370 ng/mL), respectively.

Antiviral Activity:

Pemivibart neutralized authentic SARS-CoV-2 isolates in Vero E6 or Vero E6-TMPRSS2 cells with EC50 values of 0.165-0.230 nM (24.3-34 ng/mL) against B.1, and 0.075 nM (11 ng/mL) against B.1.617.2 (Delta). For Omicron variants, EC50 values were 0.096 nM (14.2 ng/mL) against BA.1, 0.039 nM (5.8 ng/mL) against BA.2, 0.175 nM (25.8 ng/mL) against BA.4.1, 0.80-4.48 nM (118-661.2 ng/mL) against XBB.1.16, 1.97-3.25 nM (290-479.9 ng/mL) against XBB.1.5, 9.8 nM (1,445 ng/mL) against EG.5.1, and 3.59 nM (529.4 ng/mL) against HV.1 (last authentic virus variant tested).

The antiviral activity of pemivibart against historical and contemporary SARS-CoV-2 variants was evaluated using the Monogram Biosciences PhenoSense® Anti-SARS-CoV-2 Neutralizing Antibody Assay (Monogram Biosciences/LabCorp), a pseudotyped virus-like particle (VLP) assay^1. Pemivibart neutralized SARS-CoV-2 spike protein-pseudotyped VLPs representing 9 pre-Omicron variants, including B.1 and Delta (B.1.617.2), with EC50 values ranging from 0.022 to 0.083 nM (3.2 to 12.2 ng/mL). Pemivibart neutralized pseudotyped VLPs representing 45 Omicron-lineage variants, including BA.1, BA.2, BA.5, BQ.1.1, XBB.1.5, and JN.1-lineage variants, with EC50 values ranging from 0.198 to 14.3 nM (29.2 to 2,112 ng/mL). Pemivibart EC50 values against all evaluated pseudotyped VLPs representing variants of the currently dominant JN.1 lineage are presented in Table 2.

Table 2. Pemivibart Pseudotyped Virus-Like Particle Neutralization Data for Contemporary SARS‑CoV-2 Variants

Pango lineage | SARS-CoV-2 spike substitutions, insertions, and deletions relative to B.1 present in pseudotyped VLPsa | Pemivibart
Pango lineage | SARS-CoV-2 spike substitutions, insertions, and deletions relative to B.1 present in pseudotyped VLPsa | Mean EC50values ng/mL (SD)b, c | Fold-change from JN.1
Dominant Variant Circulating at Time of Emergency Use Authorization
JN.1 | Ins16MPLF, T19I, R21T, L24del, P25del, P26del, A27S, S50L, H69del, V70del, V127F, G142D, Y144del, F157S, R158G, N211del, L212I, V213G, L216F, H245N, A264D, I332V, G339H, K356T, S371F, S373P, S375F, T376A, R403K, D405N, R408S, K417N, N440K, V445H, G446S, N450D, L452W, L455S, N460K, S477N, T478K, N481K, V483del, E484K, F486P, Q498R, N501Y, Y505H, E554K, A570V, D614G, P621S, H655Y, I670V, N679K, P681R, N764K, D796Y, S939F, Q954H, N969K, P1143L | 74.6 (5.8) | 1.0d
Other Tested JN.1-lineage Spike Variants
JN.1.11.1 | Ins16MPLF, T19I, R21T, L24del, P25del, P26del, A27S, S50L, H69del, V70del, V127F, G142D, Y144del, F157S, R158G, N211del, L212I, V213G, L216F, H245N, A264D, I332V, G339H, K356T, S371F, S373P, S375F, T376A, R403K, D405N, R408S, K417N, N440K, V445H, G446S, N450D, L452W, L455S, F456L, N460K, S477N, T478K, N481K, V483del, E484K, F486P, Q498R, N501Y, Y505H, E554K, A570V, D614G, P621S, H655Y, N679K, P681R, N764K, D796Y, S939F, Q954H, N969K, V1104L, P1143L | 288.0 (64.9) | 3.9d
JN.1.13.1 | Ins16MPLF, T19I, R21T, L24del, P25del, P26del, A27S, S50L, F59S, H69del, V70del, V127F, G142D, Y144del, F157S, R158G, N211del, L212I, V213G, L216F, H245N, A264D, I332V, G339H, R346T, K356T, S371F, S373P, S375F, T376A, R403K, D405N, R408S, K417N, N440K, V445H, G446S, N450D, L452W, L455S, N460K, S477N, T478K, N481K, V483del, E484K, F486P, Q498R, N501Y, Y505H, E554K, A570V, D614G, P621S, H655Y, N679K, P681R, N764K, D796Y, S939F, Q954H, N969K, A1087S, P1143L | 220.3 (32.5) | 3.0d
JN.1.50 | Ins16MPLF, T19I, R21T, L24del, P25del, P26del, A27S, S50L, A67V, H69del, V70del, V127F, G142D, Y144del, F157S, R158G, N211del, L212I, V213G, L216F, H245N, L249F, A264D, I332V, G339H, R346T, K356T, S371F, S373P, S375F, T376A, R403K, D405N, R408S, K417N, N440K, V445P, G446S, N450D, L452W, L455S, F456L, N460K, S477N, T478K, N481K, V483del, E484K, F486P, Q498R, N501Y, Y505H, E554K, A570V, D614G, P621S, H655Y, N679K, P681R, N764K, D796Y, S939F, Q954H, N969K, P1143L | 60.3 (17.8) | 0.8d
KQ.1 | Ins16MPLF, T19I, R21T, L24del, P25del, P26del, A27S, S50L, H69del, V70del, V127F, G142D, Y144del, F157S, R158G, N211del, L212I, V213G, L216F, H245N, A264D, I332V, G339H, R346T, K356T, S371F, S373P, S375F, T376A, R403K, D405N, R408S, K417N, N440K, V445H, G446S, N450D, L452W, L455S, N460K, S477N, T478K, N481K, V483del, E484K, F486P, Q498R, N501Y, Y505H, E554K, A570V, T572I, D614G, P621S, H655Y, N679K, P681R, N764K, D796Y, S939F, Q954H, N969K, P1143L | 208.5 (30.3) | 2.8d
KP.1.1 | Ins16MPLF, T19I, R21T, L24del, P25del, P26del, A27S, S50L, H69del, V70del, V127F, G142D, Y144del, F157S, R158G, N211del, L212I, V213G, L216F, H245N, A264D, I332V, G339H, R346T, K356T, S371F, S373P, S375F, T376A, R403K, D405N, R408S, K417N, N440K, V445H, G446S, N450D, L452W, L455S, F456L, N460K, S477N, T478K, N481K, V483del, E484K, F486P, Q498R, N501Y, Y505H, E554K, A570V, D614G, P621S, H655Y, N679K, P681R, N764K, D796Y, S939F, Q954H, N969K, K1086R, V1104L, P1143L | 174.2 (28.7) | 2.3d
KP.2 | Ins16MPLF, T19I, R21T, L24del, P25del, P26del, A27S, S50L, H69del, V70del, V127F, G142D, Y144del, F157S, R158G, N211del, L212I, V213G, L216F, H245N, A264D, I332V, G339H, R346T, K356T, S371F, S373P, S375F, T376A, R403K, D405N, R408S, K417N, N440K, V445H, G446S, N450D, L452W, L455S, F456L, N460K, S477N, T478K, N481K, V483del, E484K, F486P, Q498R, N501Y, Y505H, E554K, A570V, D614G, P621S, H655Y, N679K, P681R, N764K, D796Y, S939F, Q954H, N969K, V1104L, P1143L | 154.1 (29.4) | 2.1d
KP.2.3 | Ins16MPLF, T19I, R21T, L24del, P25del, P26del, A27S, S31del, S50L, H69del, V70del, V127F, G142D, Y144del, H146Q, F157S, R158G, N211del, L212I, V213G, L216F, H245N, A264D, I332V, G339H, R346T, K356T, S371F, S373P, S375F, T376A, R403K, D405N, R408S, K417N, N440K, V445H, G446S, N450D, L452W, L455S, F456L, N460K, S477N, T478K, N481K, V483del, E484K, F486P, Q498R, N501Y, Y505H, E554K, A570V, D614G, P621S, H655Y, N679K, P681R, N764K, D796Y, S939F, Q954H, N969K, V1104L, P1143L | 305.1 (29.9) | 2.2e
KP.3 | Ins16MPLF, T19I, R21T, L24del, P25del, P26del, A27S, S50L, H69del, V70del, V127F, G142D, Y144del, F157S, R158G, N211del, L212I, V213G, L216F, H245N, A264D, I332V, G339H, K356T, S371F, S373P, S375F, T376A, R403K, D405N, R408S, K417N, N440K, V445H, G446S, N450D, L452W, L455S, F456L, N460K, S477N, T478K, N481K, V483del, E484K, F486P, Q493E, Q498R, N501Y, Y505H, E554K, A570V, D614G, P621S, H655Y, N679K, P681R, N764K, D796Y, S939F, Q954H, N969K, V1104L, P1143L | 223.0 (62.6) | 3.0d
KP.3.1.1 | Ins16MPLF, T19I, R21T, L24del, P25del, P26del, A27S, S31del, S50L, H69del, V70del, V127F, G142D, Y144del, F157S, R158G, N211del, L212I, V213G, L216F, H245N, A264D, I332V, G339H, K356T, S371F, S373P, S375F, T376A, R403K, D405N, R408S, K417N, N440K, V445H, G446S, N450D, L452W, L455S, F456L, N460K, S477N, T478K, N481K, V483del, E484K, F486P, Q493E, Q498R, N501Y, Y505H, E554K, A570V, D614G, P621S, H655Y, N679K, P681R, N764K, D796Y, S939F, Q954H, N969K, V1104L, P1143L | 239.3 (141.4) | 3.2d
KP.3.3.1 | Ins16MPLF, T19I, R21T, L24del, P25del, P26del, A27S, S50L, H69del, V70del, V127F, G142D, Y144del, F157S, R158G, N211del, L212I, V213G, L216F, H245N, A264D, I332V, G339H, K356T, S371F, S373P, S375F, T376A, R403K, D405N, R408S, K417N, N440K, V445H, G446S, N450D, L452W, L455S, F456L, N460K, S477N, T478K, N481K, V483del, E484K, F486P, Q493E, Q498R, N501Y, Y505H, T547K, E554K, A570V, D614G, P621S, H655Y, N679K, P681R, N764K, D796Y, S939F, Q954H, N969K, V1104L, P1143L | 455.0 (65.2) | 3.6e
KP 3.3.2 | Ins16MPLF, T19I, R21T, L24del, P25del, P26del, A27S, S50L, H69del, V70del, V127F, G142D, Y144del, F157S, R158G, N211del, L212I, V213G, L216F, H245N, A264D, I332V, G339H, K356T, S371F, S373P, S375F, T376A, R403K, D405N, R408S, K417N, A435S, N440K, V445H, G446S, N450D, L452W, L455S, F456L, N460K, S477N, T478K, N481K, V483del, E484K, F486P, Q493E, Q498R, N501Y, Y505H, E554K, A570V, D614G, P621S, H655Y, N679K, P681R, N764K, D796Y, S939F, Q954H, N969K, V1104L, P1143L | 496.2 (78.1) | 3.9e
LB.1 | Ins16MPLF, T19I, R21T, L24del, P25del, P26del, A27S, S31del, S50L, H69del, V70del, V127F, G142D, Y144del, F157S, R158G, Q183H, N211del, L212I, V213G, L216F, H245N, A264D, I332V, G339H, R346T, K356T, S371F, S373P, S375F, T376A, R403K, D405N, R408S, K417N, N440K, V445H, G446S, N450D, L452W, L455S, F456L, N460K, S477N, T478K, N481K, V483del, E484K, F486P, Q498R, N501Y, Y505H, E554K, A570V, D614G, P621S, H655Y, N679K, P681R, N764K, D796Y, S939F, Q954H, N969K, P1143L | 178.7 (114.1) | 2.4d
MK.3 | Ins16MPLF, T19I, R21T, L24del, P25del, P26del, A27S, S50L, H69del, V70del, V127F, G142D, Y144del, F157S, R158G, N211del, L212I, V213G, L216F, H245N, A264D, I332V, G339H, R346T, K356T, S371F, S373P, S375F, T376A, R403K, D405N, R408S, K417N, N440K, V445R, G446S, N450D, L452W, L455S, F456L, N460K, S477N, T478K, N481K, V483del, E484K, F486P, Q493E, Q498R, N501Y, Y505H, E554K, A570V, D614G, P621S, H655Y, N679K, P681R, N764K, D796Y, S939F, Q954H, N969K, V1104L, P1143L | 249.8 (43.3) | 1.9e
LP.1 | Ins16MPLF, T19I, R21T, L24del, P25del, P26del, A27S, S31del, S50L, H69del, V70del, V127F, G142D, Y144del, F157S, R158G, N211del, L212I, V213G, L216F, H245N, A264D, I332V, G339H, R346T, K356T, S371F, S373P, S375F, T376A, R403K, D405N, R408S, K417N, N440K, V445H, G446S, N450D, L452W, L455S, F456L, N460K, S477N, T478K, N481K, V483del, E484K, F486P, Q498R, N501Y, Y505H, E554K, A570V, D614G, P621S, H655Y, N679K, P681R, N764K, D796Y, S939F, Q954H, N969K, K1086R, V1104L, P1143L, M1229I | 179.4 (18.7) | 2.9e
XEC | Ins16MPLF, T19I, R21T, T22N, L24del, P25del, P26del, A27S, S50L, F59S, H69del, V70del, V127F, G142D, Y144del, F157S, R158G, N211del, L212I, V213G, L216F, H245N, A264D, I332V, G339H, K356T, S371F, S373P, S375F, T376A, R403K, D405N, R408S, K417N, N440K, V445H, G446S, N450D, L452W, L455S, F456L, N460K, S477N, T478K, N481K, V483del, E484K, F486P, Q493E, Q498R, N501Y, Y505H, E554K, A570V, D614G, P621S, H655Y, N679K, P681R, N764K, D796Y, S939F, Q954H, N969K, V1104L, P1143L | 234.7 (17.8) | 3.3e
MV.1 | Ins16MPLF, T19I, R21T, T22N, L24del, P25del, P26del, A27S, S31F, S50L, H69del, V70del, V127F, G142D, Y144del, F157S, R158G, K182N, N211del, L212I, V213G, L216F, H245N, A264D, I332V, G339H, R346T, K356T, S371F, S373P, S375F, T376A, R403K, D405N, R408S, K417N, N440K, V445H, G446S, N450D, L452W, L455S, F456V, N460K, S477N, N481K, V483del, E484K, F486P, Q498R, N501Y, Y505H, E554K, A570V, D614G, P621S, H655Y, N679K, P681R, N764K, D796Y, S939F, Q954H, N969K, P1143L | 145.3 (38.9) | 1.4e
LF.7 | Ins16MPLF, T19I, R21T, T22N, L24del, P25del, P26del, A27S, S31P, S50L, H69del, V70del, V127F, G142D, Y144del, F157S, R158G, K182R, R190S, N211del, L212I, V213G, L216F, H245N, A264D, I332V, G339H, R346T, K356T, S371F, S373P, S375F, T376A, R403K, D405N, R408S, K417N, N440K, K444R, V445H, G446S, N450D, L452W, L455S, F456L, N460K, S477N, T478K, N481K, V483del, E484K, F486P, Q498R, N501Y, Y505H, E554K, A570V, D614G, P621S, H655Y, N679K, P681R, N764K, D796Y, S939F, Q954H, N969K, P1143L | 314.6 (49.3) | 3.0e
LF.7.2.1 | Ins16MPLF, T19I, R21T, T22N, L24del, P25del, P26del, A27S, S31P, S50L, H69del, V70del, V127F, G142D, Y144del, F157S, R158G, K182R, R190S, N211del, L212I, V213G, L216F, H245N, A264D, I332V, G339H, R346T, K356T, S371F, S373P, S375F, T376A, R403K, D405N, R408S, K417N, N440K, K444R, V445H, G446S, N450D, L452W, L455S, F456L, N460K, A475V, S477N, T478K, N481K, V483del, E484K, F486P, Q498R, N501Y, Y505H, E554K, A570V, D614G, P621S, H655Y, N679K, P681R, N764K, D796Y, S939F, Q954H, N969K, P1143L | 79.5 (18.4) | 1.0e
MC.10.2 | Ins16MPLF, T19I, R21T, L24del, P25del, P26del, A27S, S31del, S50L, H69del, V70del, I101T, V127F, G142D, Y144del, F157S, R158G, N211del, L212I, V213G, L216F, H245N, A264D, I332V, G339H, K356T, S371F, S373P, S375F, T376N, R403K, D405N, R408S, K417N, N440K, V445H, G446S, N450D, L452W, L455S, F456L, N460K, S477N, T478K, N481K, V483del, E484K, F486P, Q493E, Q498R, N501Y, Y505H, E554K, A570V, D614G, P621S, H655Y, N679K, P681R, N764K, D796Y, S939F, Q954H, N969K, V1104L, P1143L | 447.9 (117.9) | 4.4e
LP.8.1 | Ins16MPLF, T19I, R21T, L24del, P25del, P26del, A27S, S31del, S50L, H69del, V70del, V127F, G142D, Y144del, F157S, R158G, F186L, R190S, N211del, L212I, V213G, L216F, H245N, A264D, I332V, G339H, R346T, K356T, S371F, S373P, S375F, T376A, R403K, D405N, R408S, K417N, N440K, V445R, G446S, N450D, L452W, L455S, F456L, N460K, S477N, T478K, N481K, V483del, E484K, F486P, Q493E, Q498R, N501Y, Y505H, E554K, A570V, D614G, P621S, H655Y, N679K, P681R, N764K, D796Y, S939F, Q954H, N969K, K1086R, V1104L, P1143L | 190.1 (43.8) | 1.9e
LP.8.1.2 | Ins16MPLF, T19I, R21T, L24del, P25del, P26del, A27S, S31del, S50L, H69del, V70del, V127F, G142D, Y144del, F157S, R158G, F186L, R190S, N211del, L212I, V213G, L216F, H245N, A264D, I332V, G339H, R346T, K356T, S371F, S373P, S375F, T376A, R403K, D405N, R408S, K417N, N440K, V445R, G446S, N450D, L452W, L455S, F456L, N460K, S477N, T478K, N481K, V483del, E484K, F486P, N487D, Q493E, Q498R, N501Y, Y505H, E554K, A570V, D614G, P621S, H655Y, N679K, P681R, N764K, D796Y, S939F, Q954H, N969K, K1086R, V1104L, P1143L | 114.6 (23.0) | 1.6e

EC50=half-maximal inhibitory concentration; Pango=Phylogenetic Assignment of Named Global Outbreak; SARS-CoV-2=severe acute respiratory syndrome coronavirus 2.

a.B.1 numbering is retained for each listed variant.

b.EC50 values for pemivibart neutralization of SARS-CoV-2 variants were determined in the Monogram Biosciences PhenoSense®Anti-SARS-CoV-2 Neutralizing Antibody Assay (Monogram Biosciences/LabCorp). In this assay, neutralization activity of the pemivibart drug product is assessed against replication-defective, luciferase-expressing, spike-pseudotyped lentivirus VLPs in human embryonic kidney (HEK) 293 cells expressing human ACE2 and transmembrane protease, serine 2 (TMPRSS2)^1. The Fact Sheet will be routinely updated as additional variant susceptibility data become available. EC50 values are reported as the mean and standard deviation from at least 3 replicates. 5,000 ng/mL was the upper concentration tested.

c.EC50 values for certain SARS-CoV-2 variants may differ from those reported by other labs and obtained under different assay conditions (EUA Summary Review, September 26, 2024).

d.Fold change in EC50 value was calculated by dividing the observed EC50 value by the average observed EC50 value for JN.1 of 74.6 ng/mL obtained from a previous experiment performed using the same pseudotyped VLP neutralization assay platform; a concurrently run JN.1 control was not available for these variants.

e.Fold change in EC50 value was calculated by dividing the observed EC50 value by the average observed EC50 value for a concurrently run JN.1 control.

Continuous evaluations remain ongoing of pemivibart neutralization susceptibility of variants that emerge and are identified through global surveillance.

Pemivibart exhibited Fc receptor and C1q binding and Fc-mediated effector activity including antibody-dependent cellular cytotoxicity (ADCC), antibody-dependent cellular phagocytosis (ADCP), and antibody-dependent complement deposition (ADCD). Cell-based complement-dependent cytolysis (CDC) was not observed using pemivibart in cell culture. Pemivibart has not been directly evaluated for antibody-dependent enhancement (ADE) of infection. The parent antibody of pemivibart (adintrevimab), which contains an identical Fc region and targets an overlapping epitope, failed to exhibit detectable ADE in cell culture.

Antiviral Resistance:

There is a potential risk of prophylaxis failure due to the emergence of a pemivibart-resistant SARS-CoV-2 variant. Prescribing healthcare providers should consider the prevalence of SARS‑CoV-2 variants in their area, where data are available, when considering prophylactic options.

Cell Culture

Data are limited regarding the scope of spike substitutions in Omicron-lineage variants that may confer significantly reduced susceptibility to pemivibart in cell culture. Escape variants were identified following serial passage of SARS-CoV-2 (Omicron XBB.1.5.6) in cell culture in the presence of pemivibart that contained a T500N spike substitution or a combination of R498Q, Y501N, and H505Y spike substitutions. Each of these substitutions is within 5 Å of the pemivibart binding interface.

Clinical Studies

The emergence of resistance is monitored in the CANOPY clinical study using genotypic (spike sequencing) and phenotypic testing (pseudotyped VLP neutralization). In the 15 successfully evaluated Cohort A cases, the SARS‑CoV‑2 variants determined based on spike amino acid sequences in participants who received pemivibart were EG.10.1 (1), JN.1 (5), KP.1.2 (1), KP.3 (2), KP.3.1.1 (5), and LP.4 (1). Resistance-associated substitutions were identified in spike sequences from 3 participants in Cohort A: T500A was detected in a JN.1 variant (100% allele frequency) and in a KP.3.1.1 variant (7% allele frequency), and T500N was detected in a KP.3.1.1 variant (15% allele frequency). These RBD amino acid substitutions occurred at a pemivibart epitope position and were associated with a 22-fold increase in EC50value (JN.1 with T500A), or no measurable neutralization (KP.3.1.1 with T500N), when spike variants carrying these substitutions were evaluated for susceptibility to pemivibart in the Monogram pseudotyped VLP assay. In the 10 successfully evaluated Cohort B cases in the pemivibart arm, SARS-CoV-2 variants determined based on spike sequences were JN.1 (1), JN.1.8.1 (1), JN.1.16 (1), KP.1.1.3 (1), KP.2 (1), KP.2.3 (1), KP.3 (2), and KP.3.1.1 (2). Resistance-associated substitutions have not been identified in Cohort B participants who received pemivibart.

Evaluations remain ongoing of pemivibart neutralization susceptibility of variants from CANOPY participants with confirmed symptomatic COVID-19.

Cross-resistance:

Cross-resistance is not expected between pemivibart and currently approved/authorized COVID‑19 therapies, including remdesivir, nirmatrelvir, or molnupiravir, since pemivibart has a distinct mechanism of action and targets a different viral protein than these drugs.

12.6 Immunogenicity

The observed incidence of anti-drug antibodies is highly dependent on the sensitivity and specificity of the assay. Differences in assay methods preclude meaningful comparisons of the incidence of anti-drug antibodies (ADA) in the studies described below with the incidence of anti-drug antibodies in other studies, including those of pemivibart.

ADAs to pemivibart were evaluated in CANOPY Cohort A and B participants through 6 months. In Cohort A, treatment-emergent (TE) ADAs were observed in 6 (2.0%) participants, including 2 (0.7%) participants on Day 28, 2 (0.7%) participants at Month 3, and 4 (1.3%) participants at Month 6. In Cohort B, TE ADAs were observed only at the Month 6 timepoint, in 3 (1.0%) participants. Because of the low occurrence of anti-drug antibodies, the effect of these antibodies on the pharmacokinetics, pharmacodynamics, safety, and/or effectiveness of pemivibart is unknown.

13 NONCLINICAL TOXICOLOGY

13.1 Carcinogenesis, Mutagenesis, Impairment of Fertility

Carcinogenicity, mutagenicity, and reproductive toxicology studies have not been conducted with pemivibart.

13.2 Animal Toxicology and/or Pharmacology

In a toxicology study in rats, pemivibart had no adverse effects when administered intravenously.

In tissue cross-reactivity studies with pemivibart using human adult and fetal tissues, no off-target binding was detected.

14 CLINICAL STUDIES

14.1 Overview of Immunobridging Approach

To support this EUA, an immunobridging approach was used to determine if PEMGARDA may be effective for pre-exposure prophylaxis of COVID-19. Immunobridging is based on the serum neutralization titer-efficacy relationships identified with other neutralizing human monoclonal antibodies against SARS-CoV-2. This includes adintrevimab, the parent mAb of pemivibart, and other mAbs that were previously authorized for EUA. To support immunobridging, serum neutralization titer was utilized to compare PEMGARDA to previous mAbs [see Clinical Pharmacology (12.2)].

14.2 Pre-exposure Prophylaxis of COVID-19 (VYD222-PREV-001 [CANOPY])

CANOPY [NCT06039449] is an ongoing clinical trial evaluating PEMGARDA for the pre-exposure prophylaxis of COVID-19 in adults ≥18 years of age in two cohorts.

- Cohort A: single-arm, open-label trial in adults who have moderate-to-severe immune compromise.
- Cohort B: placebo-controlled, randomized trial in adults who do not have moderate-to-severe immune compromise.

A total of 623 participants, 306 in Cohort A and 317 in Cohort B, received at least one dose of PEMGARDA 4500 mg in the trial. A total of 297 participants in Cohort A and 296 participants in Cohort B received a second dose of PEMGARDA 4500 mg at Month 3 redosing. Of the 162 participants who received the initial dose of placebo in Cohort B, 154 participants received a second dose of placebo at Month 3 redosing. The trial excluded participants with known or suspected SARS-CoV-2 infection within 120 days before randomization or a positive SARS-CoV-2 antigen test or RT-PCR at the time of screening. The primary data to support this EUA comes from Cohort A and is summarized below.

Participants in Cohort A were mostly female (61%), White (86%) or Black/African American (12%), and not Hispanic or Latino (94%).

The median age was 59 years, with 31% aged 65 years or older. All participants had underlying moderate-to-severe immune compromise, including:

- 65% taking high-dose corticosteroids/other immunosuppressive medications
- 13% acute leukemia, chronic lymphocytic leukemia, non-Hodgkin, lymphoma, or multiple myeloma (regardless of treatment)
- 12% primary immunodeficiency
- 11% solid organ transplant recipient
- 9% advanced HIV infection
- 7% actively treated for solid tumor or hematologic malignancies

Immunobridging Results

The primary efficacy objective of Cohort A was to evaluate protection against symptomatic COVID-19 based on calculated titers against SARS-CoV-2 following PEMGARDA administration by immunobridging to historical data from the EVADE study, which provided evidence of clinical efficacy of adintrevimab, the parent mAb of pemivibart. The primary immunobridging endpoint for Cohort A compared the ratio of the geometric mean titers between pemivibart against the relevant variant (JN.1) at Day 28 to the reference titer at Day 28. The reference titer at Day 28 was the extrapolated titer from the Day 90 adintrevimab titer [which was calculated based on Day 90 concentration of adintrevimab divided by the EC50 value against the B.1.617.2 (Delta) variant] using the half-life of pemivibart. Immunobridging would be established if the lower limit of the 2-sided 90% CI of the ratio of the geometric mean titer value is greater than 0.8.

The immunobridging results are as follows: the geometric mean ratio between the calculated titer for pemivibart against JN.1 (based on a pseudotyped VLP neutralization assay EC50 value of 74.6 ng/mL) and the calculated titer for adintrevimab against Delta (based on an authentic virus neutralization assay EC50 value of 7 ng/mL) was 0.70 (90% CI: 0.68-0.72). However, there are limitations of this analysis, including differences in the methodologies of the assays used to determine the EC50 values for pemivibart and adintrevimab against the respective variants. In an analysis using an identical cell-based assay (a pseudotyped VLP neutralization assay), for the calculated titer comparison between pemivibart against JN.1 (based on an EC50 value of 74.6 ng/mL) and adintrevimab against Delta (based on an EC50 value of 3.5 ng/mL), the geometric mean ratio was 0.35 (90% CI: 0.34-0.36).This analysis highlights the impact of even modest differences in EC50 values on the results of the primary endpoint.

In a supplementary immunobridging analysis, the titer values of pemivibart against JN.1 [see Clinical Pharmacology (12.2)]were compared, using published literature, to the titers associated with efficacy of three other SARS-CoV-2 targeting mAbs in prior clinical trials. The range of titers achieved with pemivibart for 3 months following administration of 4500 mg IV were consistent with the titer levels associated with clinical efficacy in prior clinical trials evaluating certain monoclonal antibodies for the prevention of COVID-19.

Exploratory Clinical Efficacy Results

An exploratory efficacy objective of Cohort B was to evaluate clinical efficacy of PEMGARDA compared to placebo in the prevention of RT-PCR-confirmed COVID-19 in randomized participants without SARS-CoV-2 infection at baseline and without moderate-to-severe immune compromise. Table 3 provides the results for the Cohort B exploratory clinical efficacy endpoint. Most infection events occurred during a period of time when JN.1 and variants with similar susceptibilities were dominant. No deaths or COVID-19-related hospitalizations occurred in either treatment arm of Cohort B through Month 6. PEMGARDA is not authorized for use in individuals who do not have moderate-to-severe immune compromise.

Table 3. Exploratory Clinical Efficacy Results in Randomized Participants without SARS-CoV-2 Infection at Baseline in CANOPY Cohort B (Adults who do not have Moderate-to-Severe Immune Compromise)

 | PEMGARDA n=317 | Placebo n=160
RT-PCR-confirmed symptomatic COVID-19, COVID-19-related hospitalization, or all-cause deathathrough Month 3b
Proportion: n (%) | 1 (0.3) | 8 (5.0)
Standardized Relative Risk Reduction (95% CI) | 94% (50%, 99%)
RT-PCR-confirmed symptomatic COVID-19, COVID-19-related hospitalization, or all-cause deathathrough Month 6c
Proportion: n (%) | 6 (1.9) | 19 (11.9)
Standardized Relative Risk Reduction (95% CI) | 84% (61%, 94%)

a No COVID-19-related hospitalizations or deaths occurred in either treatment arm of Cohort B through Month 6.

b Following the initial dosing period of the trial

c Cumulative through Month 6, following the initial dosing and redosing periods of the trial

An exploratory objective of Cohort A was to collect data on RT-PCR-confirmed COVID-19, COVID-19-related hospitalizations, or all-cause death in participants who received a full initial dose of study drug. Table 4 provides these results for Cohort A. No COVID-19-related hospitalizations occurred in Cohort A through Month 6. Two all-cause deaths (one due to an unknown cause and one due to suicide) occurred in Cohort A through Month 6.

Table 4. Rates of RT-PCR-confirmed COVID-19, COVID-19-Related Hospitalizations, or All-Cause Death in Participants in CANOPY Cohort A (Adults who have Moderate-to-Severe Immune Compromise)

 | PEMGARDA n=298
RT-PCR-confirmed symptomatic COVID-19, COVID-19-related hospitalization, or all-cause deathathrough Month 3b
Proportion: n (%) | 3 (1.0)
RT-PCR-confirmed symptomatic COVID-19, COVID-19-related hospitalization, or all-cause deathathrough Month 6c
Proportion: n (%) | 11 (3.7)

a No COVID-19-related hospitalizations occurred in Cohort A through Month 6. Two all-cause deaths (one due to an unknown cause and one due to suicide) occurred in Cohort A through Month 6.

b Following the initial dosing period of the trial

c Cumulative through Month 6, following the initial dosing and redosing periods of the trial

14.3 Overall Benefit-Risk Assessment and Limitations of Data Supporting the Benefits of the Product

Based on the totality of scientific evidence available, it is reasonable to believe that PEMGARDA may be effective for pre-exposure prophylaxis of COVID-19 caused by susceptible SARS-CoV-2 variants in the authorized population [see Microbiology (12.4)]. The calculated pemivibart serum neutralizing antibody titers for the JN.1 variant were consistent with the titer levels associated with efficacy in prior clinical trials of adintrevimab and certain other monoclonal antibody products previously authorized for the prevention of COVID-19. The exploratory clinical results from Cohort B of CANOPY also provide support that PEMGARDA may be effective for pre-exposure prophylaxis of COVID-19 caused by the JN.1 variant and other similarly susceptible SARS-CoV-2 variants in the authorized use population.

There are limitations of the immunobridging data supporting the benefits of PEMGARDA. Evidence of clinical efficacy for other neutralizing human monoclonal antibodies against SARS-CoV-2 was based on different populations and SARS-CoV-2 variants that are no longer circulating. Additionally, the variability associated with cell-based EC50value determinations across laboratories, along with limitations related to PK data and efficacy estimates for the mAbs in prior clinical trials, impact the ability to precisely estimate protective titer ranges. The potential benefits of PEMGARDA for pre-exposure prophylaxis of COVID-19 caused by variants other than JN.1 may vary based on variant susceptibility and national variant frequencies [see Microbiology (12.4)].

The totality of scientific evidence, including the available clinical and pharmacokinetic data along with the nonclinical viral neutralization data provided from Monogram in Microbiology (12.4), support the potential benefit of PEMGARDA in the authorized patient population.

15 REFERENCES

1. Huang et al. Calibration of two validated SARS-CoV-2 pseudovirus neutralization assays for COVID-19 vaccine evaluation; Sci Rep. 2021; 11:23921; [https://doi.org/10.1038/s41598-021-03154-6]).

16 HOW SUPPLIED/STORAGE AND HANDLING

PEMGARDA injection is a sterile, preservative-free, clear to slightly opalescent, colorless to yellow solution supplied in a single-dose 6R vial intended for intravenous infusion only.

Antibody | Concentration | Package Size | NDC
Pemivibart | 500 mg/4 mL vial (125 mg/mL) | Nine vials per carton | 81960-031-03

Refrigerate unopened vials at 2 ℃ to 8 °C (36 ℉ to 46 °F) in the original carton to protect from light.

Do not freeze or shake. Do not use if seal is broken or missing.

17 PATIENT COUNSELING INFORMATION

As a prescribing healthcare practitioner, you must communicate to the patient, parent, and caregiver information consistent with the “FACT SHEET FOR PATIENTS, PARENTS OR CAREGIVERS” and provide them with a copy of this Fact Sheet prior to administration of PEMGARDA.

Anaphylaxis

Inform individuals that anaphylaxis has been observed with PEMGARDA. Advise individuals that they will be monitored during and for at least two hours after completion of the infusion. In those who experience signs or symptoms of anaphylaxis, PEMGARDA use will be discontinued permanently [see Boxed Warnings, and Warnings and Precautions (5.1)].

Hypersensitivity and Infusion-Related Reactions

Inform individuals that hypersensitivity and infusion-related reactions have occurred during the infusion and up to 24 hours after the infusion with PEMGARDA. These hypersensitivity or infusion-related reactions may be severe or life threatening. Inform individuals that they will be monitored during and for at least two hours after completion of the infusion for signs and symptoms of hypersensitivity [see Warnings and Precautions (5.2)].

Dosing

Inform individuals that they may need to receive additional doses of PEMGARDA every 3 months if ongoing protection is needed [see Dosage and Administration (2) and Clinical Pharmacology (12)].

Risk for COVID-19 Due to SARS-CoV-2 Viral Variants With Substantially Reduced Susceptibility to PEMGARDA

Certain SARS-CoV-2 viral variants may emerge that have substantially reduced susceptibility to PEMGARDA. PEMGARDA may not be effective at preventing COVID-19 caused by these SARS‑CoV-2 viral variants. Inform individuals of the increased risk, compared to other variants, for COVID-19 due to SARS-CoV-2 viral variants that exhibit substantially reduced susceptibility to PEMGARDA. If signs or symptoms of COVID-19 occur, advise individuals to test for COVID‑19 and seek medical attention, including starting treatment for COVID-19 as appropriate [see Warnings and Precautions (5.4)].

18 MANUFACTURER INFORMATION

For additional information, visit: http://www.pemgarda.com/or scan the code below:

Manufactured and distributed by:

Invivyd, Inc.

1601 Trapelo Road, Suite 178

Waltham, MA 02451

INVIVYD™, PEMGARDA™, and the Ribbon logos are trademarks of Invivyd, Inc.

©2024 Invivyd, Inc. All rights reserved.

Revised 05/2025

FACT SHEET FOR PATIENTS, PARENTS, AND CAREGIVERS

What is the most important information I should know about PEMGARDA?

PEMGARDA may cause serious side effects, including:

- A serious allergic reaction called anaphylaxis.Anaphylaxis can be life-threatening and can happen during or after your infusion of PEMGARDA. In case you have a severe allergic reaction to PEMGARDA and need medical help right away, you will receive PEMGARDA in a healthcare setting. Your healthcare provider will monitor you for allergic reactions during your infusion and for at least 2 hours after you are finished receiving PEMGARDA. Your healthcare provider will stop PEMGARDA right away if you develop signs or symptoms of anaphylaxis or severe allergic reaction. Tell your healthcare provider right away if you get any of the following signs or symptoms of anaphylaxis during or after your infusion of PEMGARDA:

itching | dizziness
flushing | ringing in ears
hives | wheezing
skin redness | trouble breathing
swelling of your face, lips, mouth, tongue, throat, hands, or feet | chest discomfort
sweating | fast heartbeat

See “What are the important possible side effects of PEMGARDA?”for more information about side effects.

You are being given this Fact Sheet because your healthcare provider believes it is necessary to provide you or your child with PEMGARDA for pre-exposure prophylaxis to help prevent coronavirus disease 2019 (COVID‑19) caused by the SARS-CoV-2 virus.

This Fact Sheet contains information to help you understand the potential risks and the potential benefits of receiving PEMGARDA, which you, or your child, have received or may receive.

The United States (US) Food and Drug Administration (FDA) has issued an Emergency Use Authorization (EUA) to make PEMGARDA available during the COVID-19 pandemic (for more details about an EUA please see “ What is an Emergency Use Authorization (EUA)?” at the end of this document). PEMGARDA is not an FDA-approved medicine in the US.

Read this Fact Sheet for information about PEMGARDA. Talk to your healthcare provider about your options or if you have any questions. It is your choice for you or your child to receive PEMGARDA or stop at any time.

What is COVID-19?

COVID-19 is caused by a virus called a coronavirus (SARS-CoV-2). You can get COVID-19 through contact with another person who has the virus.

COVID-19 illnesses have ranged from very mild (including some with no reported symptoms) to severe, including illness resulting in death. While information so far suggests that most COVID‑19 illnesses are mild, serious illness can happen and may cause some of your other medical conditions to become worse. Older people and people of all ages with severe, long lasting (chronic) medical conditions like immune compromise, heart disease, lung disease, diabetes, and obesity, for example, seem to be at higher risk of being hospitalized for COVID‑19.

What is PEMGARDA?

PEMGARDA is an investigational medicine that is used for pre-exposure prophylaxis to help prevent COVID-19 in adults and children 12 years of age and older who weigh at least 88 pounds (40 kg) who:

- are notcurrently infected with SARS-CoV-2 and who have notbeen known to be exposed to someone who is infected with SARS-CoV-2 and
- have moderate-to-severe immune compromise because of a medical condition or because they receive medicines or treatments that suppress the immune system andthey are unlikely to have an adequate response to COVID-19 vaccination.

PEMGARDA is investigational because it is still being studied. There is limited information about the safety and effectiveness of using PEMGARDA for prevention of COVID-19. The FDA has authorized the emergency use of PEMGARDA for pre-exposure prophylaxis to help prevent COVID-19 under an EUA. For more information on EUA, see the “What is an Emergency Use Authorization (EUA)?” section at the end of this Fact Sheet.

PEMGARDA is notauthorized:

- to treat COVID-19
- to prevent COVID-19 after being around someone infected with SARS-CoV-2 (post-exposure prophylaxis)
- when PEMGARDA is not expected to work against more than 90% of the SARS- CoV-2 variants in the US. Viruses can change over time (mutate) and develop into a slightly different form of the virus, called a variant.
- for use in children under 12 years of age or weighing less than 88 pounds (40 kg)

Pre-exposure prophylaxis to help prevent COVID-19 with PEMGARDA does not take the place of receiving COVID-19 vaccination in people who can be vaccinated for COVID-19. If your health care provider recommends it, you should receive a COVID-19 vaccination.

If you have received a COVID-19 vaccine, you should wait at least 2 weeks after vaccination to receive PEMGARDA.

What should I tell my healthcare provider before I receive PEMGARDA?

Tell your healthcare provider about all of your medical conditions, including if you:

- have any allergies, including if you have had a severe allergic reaction to a COVID‑19 vaccine or to PEMGARDA.
- are pregnant or plan to become pregnant. It is not known if PEMGARDA can harm your unborn baby.
- are breastfeeding or plan to breastfeed. It is not known if PEMGARDA can pass into your breast milk. Talk to your healthcare provider about the best way to feed your baby if you receive PEMGARDA.
- have any serious illnesses.
- take any medicines including prescription, over-the-counter, vitamins, and herbal products.

How will I receive PEMGARDA?

- You will receive 1 dose of PEMGARDA.
- PEMGARDA will be given to you through an infusion in a vein (intravenous [IV] infusion). It will take about 60 minutes to finish the infusion.
- You will receive PEMGARDA in a healthcare setting.
- You will be observed by a healthcare provider during your infusion and for at least 2 hours after your infusion is finished.

You may need to receive additional doses of PEMGARDA for ongoing protection from COVID-19. Viruses can change over time (mutate) and develop into a slightly different form of the virus, called a variant. Based on what we know about current SARS-CoV-2 variants, you may need to receive additional doses of PEMGARDA every 3 months.

Who should generally not take PEMGARDA?

Do not take PEMGARDA if you have had a severe allergic reaction to PEMGARDA or any ingredient in PEMGARDA. See the end of this Fact Sheet for a complete list of ingredients in PEMGARDA.

What are the important possible side effects of PEMGARDA?

- See “ What is the most important information I should know about PEMGARDA?”
- Allergic and infusion-related reactions.Allergic and infusion-related reactions are common and can sometimes be severe or life-threatening. Allergic and infusion-related reactions can happen during and after your infusion of PEMGARDA. You may have an increased risk of allergic reaction with PEMGARDA if you have had a severe allergic reaction to a COVID‑19 vaccine. PEMGARDA contains polysorbate 80, an ingredient in some COVID‑19 vaccines. Also, polysorbate 80 is similar to polyethylene glycol (PEG), an ingredient in other COVID‑19 vaccines. Your healthcare provider may consult with a healthcare provider who specializes in allergy and immunology before giving you PEMGARDA if you have had a serious allergic reaction to a COVID-19 vaccine. Your healthcare provider will monitor you for allergic reactions during the infusion and for at least 2 hours after you receive PEMGARDA. Tell your healthcare provider right away if you get any of the following signs or symptoms of an allergic or infusion-related reaction during or after your infusion of PEMGARDA:

fever | headache
trouble breathing or shortness of breath | throat tightness or irritation
chills | high or low blood pressure
tiredness | swelling of your face, lips, mouth, tongue, throat, hands, or feet
fast or slow heart rate | rash, including hives
chest pain or discomfort | itching
weakness | muscle aches
confusion | feeling lightheaded, faint, or dizzy
nausea | sweating

The side effects of receiving any medicine by vein (IV) may include pain, redness, bleeding, bruising of the skin, soreness, swelling, and possible infection at the infusion site.

The most common side effects in people treated with PEMGARDAwho have moderate-to-severe immune compromise include allergic and infusion-related reactions, infusion site reactions, common cold, viral infection, flu-like illness, tiredness, headache and nausea.

These are not all the possible side effects of PEMGARDA. Not a lot of people have been given PEMGARDA. Serious and unexpected side effects may happen. PEMGARDA is still being studied, so it is possible that all of the risks are not known at this time.

What other important information do I need to know when receiving PEMGARDA?

Risk of COVID-19 caused by certain SARS-CoV-2 variants:Viruses can change over time (mutate) and develop into a slightly different form of the virus, called a variant. PEMGARDA may not prevent COVID-19 caused by certain SARS‑CoV-2 variants. If you are exposed to these variants, your chance of developing COVID-19 is higher than from other variants. Tell your healthcare provider right away, and test for COVID-19, if you develop any symptoms of COVID-19, including:

fever or chills | headache
cough | sore throat
shortness of breath or difficulty breathing | new loss of taste or smell
congestion or runny nose | feeling tired (fatigue)
nausea or vomiting | muscle or body aches
diarrhea

For more information about the symptoms of COVID-19, go to https://www.cdc.gov/coronavirus/2019-ncov/symptoms-testing/symptoms.html.

If you develop COVID-19, your healthcare provider may recommend one of the available COVID-19 treatments.

What other prevention choices are there?

Vaccines to help prevent COVID-19 are approved or available under Emergency Use Authorization. Use of PEMGARDA does not replace vaccination against COVID-19. For more information about other medicines authorized for treatment or prevention of COVID-19, go to https://www.fda.gov/emergency-preparedness-and-response/mcm- legal-regulatory-and-policy-framework/emergency-use-authorization#coviddrugs.

It is your choice to receive or not receive PEMGARDA for pre-exposure prophylaxis to help prevent COVID-19. Should you decide not to receive PEMGARDA, it will not change your standard medical care.

PEMGARDA is not authorized to treat COVID-19 or for post-exposure prophylaxis of COVID-19.

What if I am pregnant or breastfeeding?

There is no experience using PEMGARDA in women who are pregnant or breastfeeding. For a mother and unborn baby, the benefit of receiving PEMGARDA may be greater than the risk of using the product. If you are pregnant or breastfeeding, discuss your options and specific situation with your healthcare provider.

How do I report side effects with PEMGARDA?

Tell your healthcare provider right away if you have any side effect that bothers you or does not go away. Report side effects to FDA MedWatch at www.fda.gov/medwatch, or call 1‑800‑FDA‑1088, or call Invivyd at 1-800-890-3385.

How can I learn more about PEMGARDA?

If you have questions, visit the website, or call the telephone number provided below. To access the most recent PEMGARDA Fact Sheet, please scan the QR code provided below.

Website | Telephone Number
www.Pemgarda.com | 1-800-890-3385

How can I learn more about COVID-19?

- Ask your healthcare provider.
- Visit https://www.cdc.gov/COVID19.
- Contact your local or state public health department.

What is an Emergency Use Authorization?

The United States FDA has made PEMGARDA available under an emergency access mechanism called an Emergency Use Authorization (EUA). The EUA is supported by a Secretary of Health and Human Services (HHS) declaration under the Federal Food, Drug, and Cosmetic Act that circumstances exist to justify the emergency use of drugs and biological products during the COVID-19 pandemic.

PEMGARDA for pre-exposure prophylaxis to help prevent COVID-19 has not undergone the same type of review as an FDA-approved product. In issuing an EUA the FDA has determined, among other things, that based on the total amount of scientific evidence available, including data from adequate and well-controlled clinical trials, it is reasonable to believe that the product may be effective for preventing COVID‑-19, or a serious or life-threatening disease or condition caused by COVID-19; that the known and potential benefits of the product, when used to prevent such disease or condition, outweigh the known and potential risks of such product; and that there are no adequate, approved, and available alternatives.

All of these criteria must be met to allow the product to be used during the COVID-19 pandemic. The EUA for PEMGARDA is in effect for the duration of the COVID-19 HHS declaration justifying emergency use of PEMGARDA, unless terminated or revoked (after which PEMGARDA may no longer be used under the EUA).

What are the ingredients in PEMGARDA?

Active ingredient: pemivibart

Inactive ingredients: glycine, L-arginine hydrochloride, L-histidine, L-histidine hydrochloride monohydrate, L-methionine, polysorbate 80, and sterile water for injection.

Manufactured and distributed by: Invivyd, Inc., 1601 Trapelo Road, Suite 178, Waltham, MA 02451

INVIVYD™, PEMGARDA™, and the Ribbon logos are trademarks of Invivyd, Inc.

©2024 Invivyd, Inc. All rights reserved.

Revised: August 2024

Emergency Use Authorization (EUA) of PEMGARDA (pemivibart) for Coronavirus Disease 2019 (COVID-19)

RECENT MAJOR CHANGES

Microbiology (12.4): Updated viral resistance data 02/2025

Immunogenicity (12.6): Updated with anti-drug antibody data 02/2025

PRINCIPAL DISPLAY PANEL - 500 MG/4 ML CARTON

NDC 81960-031-03

Rx-Only

PEMGARDA

(pemivibart) injection

500 mg/4 mL (125 mg/mL)

For use under Emergency Use Authorization (EUA).

For Intravenous Infusion only.

Refer to the FDA-authorized Fact Sheet for detailed instructions on dosage and administration.